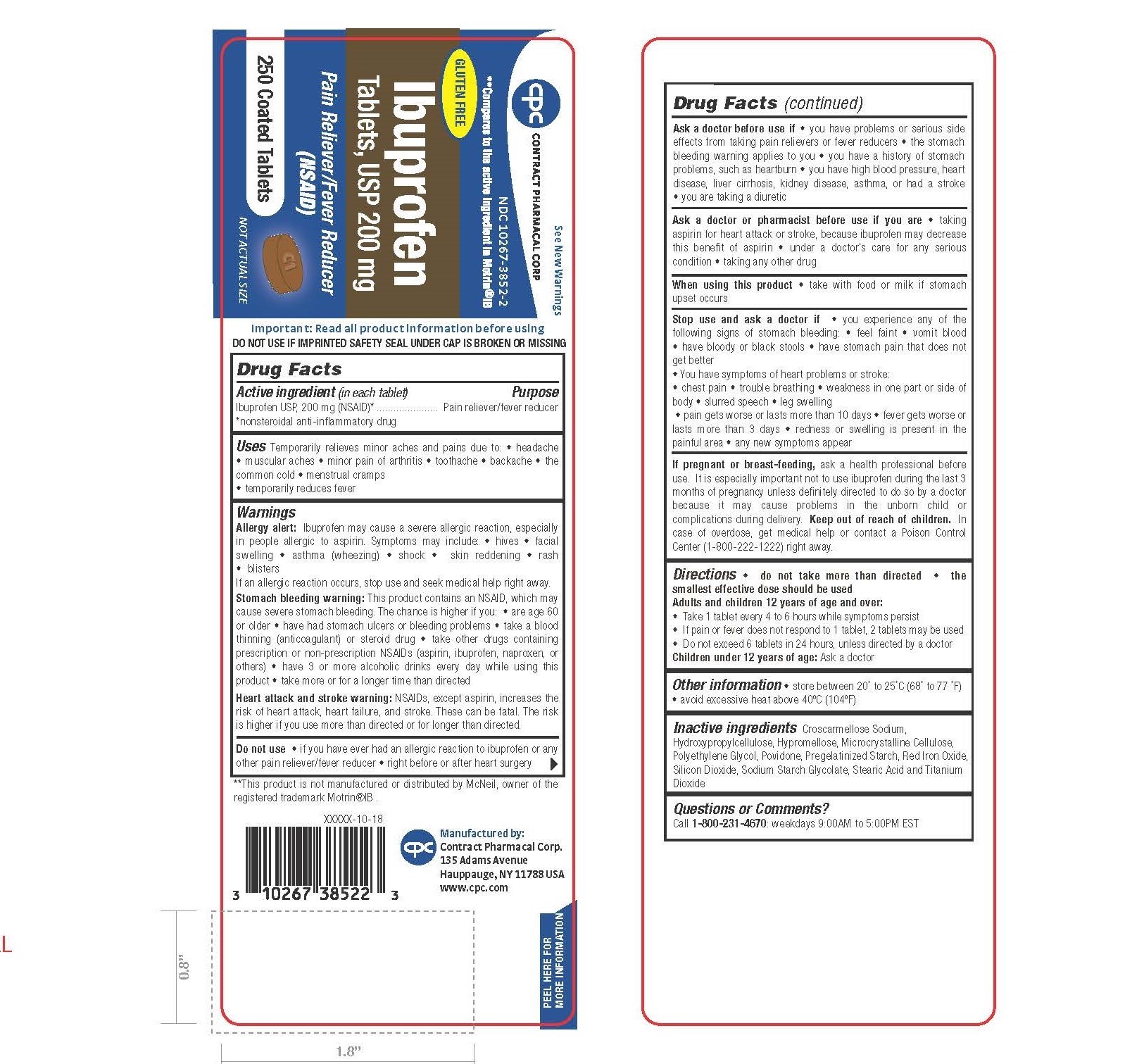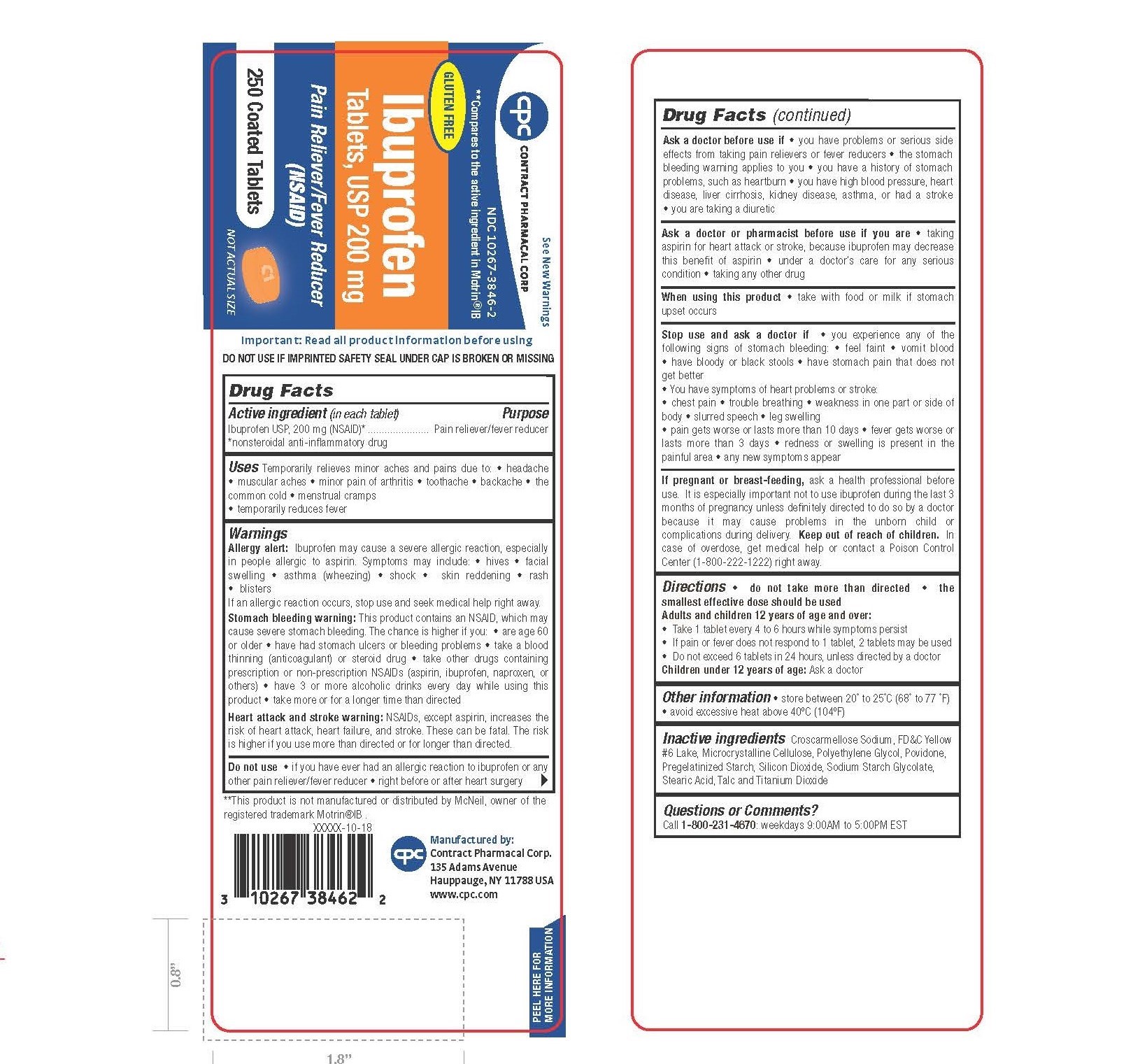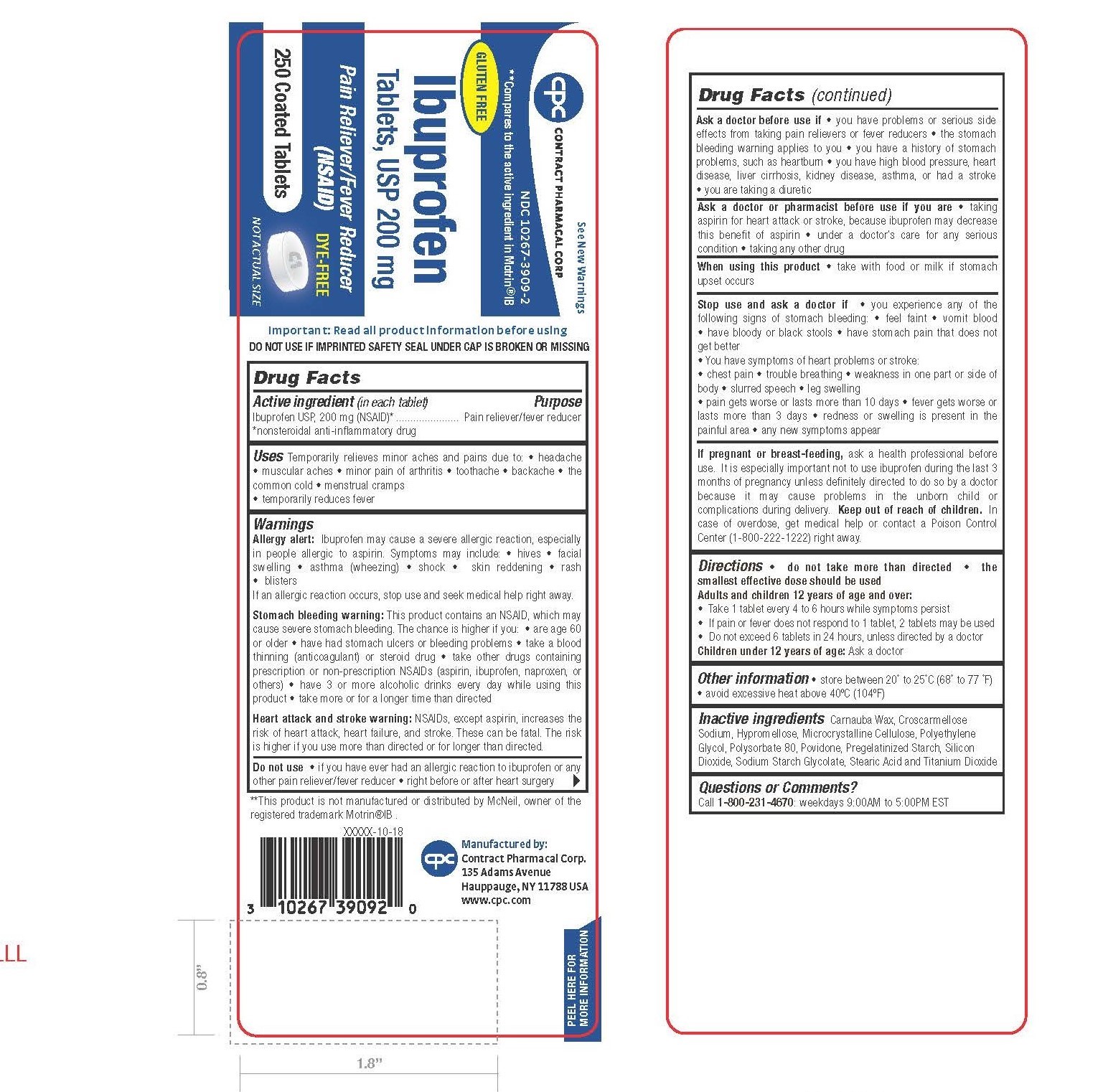 DRUG LABEL: ibuprofen
NDC: 10267-3852 | Form: TABLET
Manufacturer: Contract Pharmacal Corp.
Category: otc | Type: HUMAN OTC DRUG LABEL
Date: 20181107

ACTIVE INGREDIENTS: IBUPROFEN 200 mg/1 1
INACTIVE INGREDIENTS: CROSCARMELLOSE SODIUM; STARCH, CORN; CELLULOSE, MICROCRYSTALLINE; STEARIC ACID; SODIUM STARCH GLYCOLATE TYPE A CORN; POVIDONE K30; SILICON DIOXIDE; FERRIC OXIDE RED; TITANIUM DIOXIDE; POLYETHYLENE GLYCOL 400; HYDROXYPROPYL CELLULOSE, UNSPECIFIED; HYPROMELLOSES

3852, 3846, 3909

Important: Read all product information before using.
DO NOT USE IF IMPRINTED SAFETY SEAL UNDER CAP IS BROKEN OR MISSING.

Drug Facts

ACTIVE INGREDIENT (in each tablet)

Ibuprofen USP, 200 mg (NSAID)*

*nonsteroidal anti-inflammatory drug

PURPOSE

Pain reliever/fever reducer

USES

Temporarily relieves minor aches and pains due to:

- headache
- muscular ache
- minor pain of arthritis
- toothache
- backache
- the common cold
- menstrual cramps
- temporarily reduces fever

WARNINGS

Allergy alert: Ibuprofen may cause a severe allergic reaction, especially in people allergic to aspirin. Symptoms may include:

- hives
- facial swelling
- asthma (wheezing)
- shock
- skin reddening
- rash
- blisters

If an allergic reaction occurs, stop use and seek medical help right away.

Stomach bleeding warning: This product contains an NSAID, which may cause severe stomach bleeding. The chance is higher if you:

- are age 60 or older
- have had stomach ulcers or bleeding problems
- take a blood thinning (anticoagulant) or steroid drug
- take other drugs containing prescription or non-prescription NSAIDs (aspirin, ibuprofen, naproxen, or others)
- have 3 or more alcoholic drinks every day while using this product
- take more or for longer time than directed

Heart attack and stroke warning: NSAIDs, except aspirin, increases the risk of heart attack, heart failure, and stroke. These can be fatal. The risk is higher if you use more than directed or for longer than directed.

DO NOT USE

- if you have ever had an allergic reaction to ibuprofen or any other pain reliever/fever reducer
- right before or after heart surgery

ASK DOCTOR before use if

- you have problems or serious side effects from taking pain relievers or fever reducers
- the stomach bleeding warning applies to you
- you have a history of stomach problems such as heartburn
- you have high blood pressure, heart disease, liver cirrhosis, kidney disease, asthma, or had a stroke
- you are taking a diuretic

ASK A DOCTOR OR PHARMACIST before use if you are

- taking aspirin for heart attack or stroke, because ibuprofen may decrease this benefit of aspirin
- under a doctor’s care for any serious condition
- taking any other drug

WHEN USING this product

- take with food or milk if stomach upset occurs

STOP USE and ask a doctor if

- you experience and of the following signs of stomach bleeding:
  - feel faint
  - vomit blood
  - have bloody or black stools
  - have stomach pain that does not get better
  - You have symptoms of heart problems or stroke:
- chest pain
- trouble breathing
- weakness in one part or side of body
- slurred speech
- leg swelling

- pain gets worse or lasts more than 10 days
- fever gets worse or lasts more than 3 days
- redness or swelling is present in the painful area
- any new symptoms appear

If PREGNANT OR BREAST FEEDING

ask a health professional before use. It is especially important not to use ibuprofen during the last 3 months of pregnancy unless definitely directed to do so by a doctor because it may cause problems in the unborn child or complications during delivery.

KEEP OUT OF REACH OF CHILDREN

In case of overdose, get medical help or contact a Poison Control Center (1-800-222-1222) right away.

DIRECTIONS

- do not take more than directed
- the smallest effective dose should be used

Adults and children 12 years of age and over:

■ Take 1 tablet every 4 to 6 hours while symptoms persist ■ If pain or fever does not respond to 1 tablet, 2 tablets may be used ■ Do not exceed 6 tablets in 24 hours, unless directed by a doctor

Children under 12 years of age: ■ Ask a doctor

Other information

- store between 20˚ to 25˚C (68˚to 77˚F)
- avoid excessive heat above 40˚C (104˚F)

INACTIVE INGREDIENTS

(White) Carnauba Wax, Croscarmellose Sodium, Hypromellose, Microcrystalline Cellulose, Polyethylene Glycol, Polysorbate 80, Povidone, Pregelatinized Starch, Silicon Dioxide, Sodium Starch Glycolate, Stearic Acid, and Titanium Dioxide.

(Orange) Croscarmellose Sodium, FD&C Yellow #6 Lake, Microcrystalline Cellulose, Polyethylene Glycol, Povidone, Pregelatinized Starch, Silicon Dioxide, Sodium Starch Glycolate, Stearic Acid, Talc and Titanium Dioxide.

(Brown) Croscarmellose Sodium, Hydroxypropylcellulose, Hypromellose, Microcrystalline Cellulose, Polyethylene Glycol, Povidone, Pregelatinized Starch, Red Iron Oxide, Silicon Dioxide, Sodium Starch Glycolate, Stearic Acid, and Titanium Dioxide.

QUESTIONS or COMMENTS?

Call 1-800-231-4670: weekdays 9:00 AM to 5:00 PM EST

**This product is not manufactured or distributed by McNeil, owner of the registered trademark Motrin®IB

Manufactured by:
Contract Pharmacal Corp.
135 Adams Avenue
Hauppauge, NY 11788 USA
www.cpc.com

XXXXX-10-18

Barcode

Peel here for more information

PACKAGE LABEL.PRINCIPAL DISPLAY PANEL

See New Warnings
CONTRACT PHARMACAL CORP NDC 10267-3909-2
**Compares to the active ingredient in Motrin®IB

GLUTEN FREE

Ibuprofen Tablets, USP 200 mg
Pain Reliever/Fever Reducer
(NSAID)
250 Coated Tablets
DYE-FREE
NOT ACTUAL SIZE

See New Warnings

CONTRACT PHARMACAL CORP NDC 10267-3846-2
**Compares to the active ingredient in Motrin®IB
GLUTEN FREE

Ibuprofen Tablets, USP 200 mg
Pain Reliever/Fever Reducer
(NSAID)
250 Coated Tablets
NOT ACTUAL SIZE

See New Warnings

CONTRACT PHARMACAL CORP NDC 10267-3852-2
**Compares to the active ingredient in Motrin®IB
GLUTEN FREE

Ibuprofen Tablets, USP 200 mg
Pain Reliever/Fever Reducer
(NSAID)
250 Coated Tablets
NOT ACTUAL SIZE